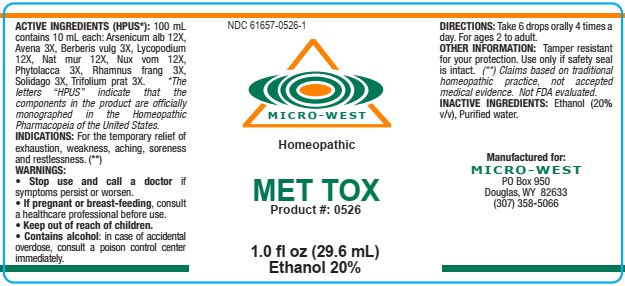 DRUG LABEL: Met-Tox
NDC: 61657-0526 | Form: LIQUID
Manufacturer: wHITE mANUFACTURING INC DBA MICRO-WEST
Category: homeopathic | Type: HUMAN OTC DRUG LABEL
Date: 20210121

ACTIVE INGREDIENTS: ARSENIC TRIOXIDE 12 [hp_X]/30 mL; AVENA SATIVA FLOWERING TOP 3 [hp_X]/30 mL; BERBERIS VULGARIS ROOT BARK 3 [hp_X]/30 mL; LYCOPODIUM CLAVATUM SPORE 12 [hp_X]/30 mL; SODIUM CHLORIDE 12 [hp_X]/30 mL; STRYCHNOS NUX-VOMICA SEED 12 [hp_X]/30 mL; PHYTOLACCA AMERICANA ROOT 3 [hp_X]/30 mL; FRANGULA ALNUS BARK 3 [hp_X]/30 mL; SOLIDAGO VIRGAUREA FLOWERING TOP 3 [hp_X]/30 mL; TRIFOLIUM PRATENSE FLOWER 3 [hp_X]/30 mL; IRON 12 [hp_X]/30 mL; MAGNESIUM 12 [hp_X]/30 mL; SULFUR 12 [hp_X]/30 mL; CHROMIUM 12 [hp_X]/30 mL; ALUMINUM 12 [hp_X]/30 mL; CALCIUM 12 [hp_X]/30 mL; ACTIVATED CHARCOAL 12 [hp_X]/30 mL; SILICON 12 [hp_X]/30 mL; SELENIUM 12 [hp_X]/30 mL; ZINC 12 [hp_X]/30 mL; BORON 12 [hp_X]/30 mL; COBALT 12 [hp_X]/30 mL; BERYLLIUM 12 [hp_X]/30 mL; TIN 12 [hp_X]/30 mL; ANTIMONY 12 [hp_X]/30 mL; CERIUM 12 [hp_X]/30 mL; CESIUM 12 [hp_X]/30 mL; ARSENIC 12 [hp_X]/30 mL; ZIRCONIUM 12 [hp_X]/30 mL; STRONTIUM 12 [hp_X]/30 mL; NEODYMIUM 12 [hp_X]/30 mL; LEAD 12 [hp_X]/30 mL; CHLORIDE ION 12 [hp_X]/30 mL; LITHIUM 12 [hp_X]/30 mL; COPPER 12 [hp_X]/30 mL; BROMINE 12 [hp_X]/30 mL; SODIUM 12 [hp_X]/30 mL; YTTRIUM 12 [hp_X]/30 mL; IODINE 12 [hp_X]/30 mL; GADOLINIUM 12 [hp_X]/30 mL; FLUORIDE ION 12 [hp_X]/30 mL; SAMARIUM 12 [hp_X]/30 mL; CADMIUM 12 [hp_X]/30 mL; DYSPROSIUM 12 [hp_X]/30 mL; MERCURY 12 [hp_X]/30 mL; TITANIUM 12 [hp_X]/30 mL; POTASSIUM 12 [hp_X]/30 mL; RUBIDIUM 12 [hp_X]/30 mL; ERBIUM 12 [hp_X]/30 mL; VANADIUM 12 [hp_X]/30 mL; SCANDIUM 12 [hp_X]/30 mL; RUTHENIUM 12 [hp_X]/30 mL; LUTETIUM 12 [hp_X]/30 mL; HOLMIUM 12 [hp_X]/30 mL; PRASEODYMIUM 12 [hp_X]/30 mL; TERBIUM 12 [hp_X]/30 mL; BARIUM 12 [hp_X]/30 mL; TELLURIUM 12 [hp_X]/30 mL; NIOBIUM 12 [hp_X]/30 mL; PALLADIUM 12 [hp_X]/30 mL; HAFNIUM 12 [hp_X]/30 mL; TANTALUM 12 [hp_X]/30 mL; MOLYBDENUM 12 [hp_X]/30 mL; EUROPIUM 12 [hp_X]/30 mL; GALLIUM 12 [hp_X]/30 mL; GOLD 12 [hp_X]/30 mL; OSMIUM 12 [hp_X]/30 mL; PLATINUM 12 [hp_X]/30 mL; RHODIUM 12 [hp_X]/30 mL; INDIUM 12 [hp_X]/30 mL; SILVER 12 [hp_X]/30 mL; THORIUM 12 [hp_X]/30 mL; IRIDIUM 12 [hp_X]/30 mL; HYDROGEN 12 [hp_X]/30 mL; NITROGEN 12 [hp_X]/30 mL; YTTERBIUM 12 [hp_X]/30 mL
INACTIVE INGREDIENTS: ALCOHOL

DRUG FACTS

ACTIVE INGREDIENTS

ARSENICUM ALBUM 12X

AVENA SATIVA 3X
BERBERIS VULGARIS 3X

LYCOPODIUM CLAVATUM 12X

NATRUM MURIATICUM 12X

NUX VOMICA 12X

PHYTOLACCA DECANDRA 3X

RHAMNUS FRANGULA 3X

SOLIDAGO VIRGAUREA 3X

TRIFOLIUM PRATENSE 3X

PURPOSE

FOR THE TEMPORARY RELIEF OF EXHAUSTION, WEAKNESS, ACHING, SORENESS AND RESTLESSNESS

KEEP OUT OF REACH OF CHILDREN

OTHER INFORMATION

TAMPER RESISTANT FOR YOUR PROTECTION. USE ONLY IF SEAL IS INTACT

INDICATIONS AND USAGE

INDICATIONS: FOR THE TEMPORARY RELIEF OF EXHAUSTION, WEAKNESS, ACHING, SORENESS AND RESTLESSNESS

WARNINGS

WARNING:STOP USE AND CALL A DOCTOR IF SYMPTOMS PERSIST OR WORSEN. IF PREGNANT OR BREAST FEEDING, CONSULT A HEALTHCARE PROFESSIONAL BEFORE USE. CONTAINS ALCOHOL: IN CASE OF ACCIDENTAL OVERDOSE, CONSULT A POISON CONTROL CENTER IMMEDIATELY

DIRECTIONS

DIRECTIONS:TAKE 6 DROPS ORALLY, 4 TIMES A DAY. FOR AGES 2 TO ADULT

INACTIVE INGREDIENT

ALCOHOL (20% V/V) PURIFIED WATER

MANUFACTURE

MANUFACTURED FOR MICRO-WEST

P.O. BOX 950

DOUGLAS, WY 82633

1-307-358-5066

PACKAGE LABEL

NDC 61657-0526-1

MICRO-WEST

Homeopathic

MET TOX

Product #: 0526

1.0 fl oz. (29.6 mL)

Ethanol 20%